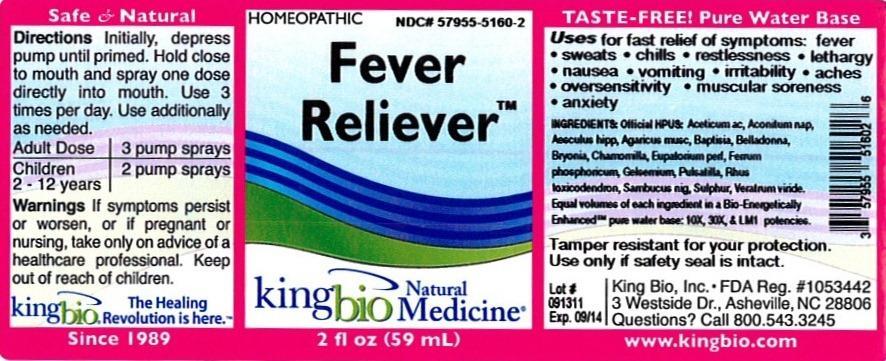 DRUG LABEL: Fever Reliever
NDC: 57955-5160 | Form: LIQUID
Manufacturer: King Bio Inc.
Category: homeopathic | Type: HUMAN OTC DRUG LABEL
Date: 20121002

ACTIVE INGREDIENTS: ACETIC ACID 10 [hp_X]/59 mL; ACONITUM NAPELLUS 10 [hp_X]/59 mL; AMANITA MUSCARIA VAR. MUSCARIA FRUITING BODY 10 [hp_X]/59 mL; BAPTISIA TINCTORIA ROOT 10 [hp_X]/59 mL; ATROPA BELLADONNA 10 [hp_X]/59 mL; BRYONIA ALBA ROOT 10 [hp_X]/59 mL; MATRICARIA RECUTITA 10 [hp_X]/59 mL; EUPATORIUM PERFOLIATUM FLOWERING TOP 10 [hp_X]/59 mL; FERROSOFERRIC PHOSPHATE 10 [hp_X]/59 mL; GELSEMIUM SEMPERVIRENS ROOT 10 [hp_X]/59 mL; PULSATILLA VULGARIS 10 [hp_X]/59 mL; TOXICODENDRON PUBESCENS LEAF 10 [hp_X]/59 mL; SAMBUCUS NIGRA FLOWERING TOP 10 [hp_X]/59 mL; SULFUR 10 [hp_X]/59 mL; VERATRUM VIRIDE ROOT 10 [hp_X]/59 mL; HORSE CHESTNUT 10 [hp_X]/59 mL
INACTIVE INGREDIENTS: WATER

Fever Reliever

Active Ingredients

Offiicial HPUS: Aceticum acidum, Aconitum napellus, Aesculus Hippocastanum, Agarecus muscarius, Baptisia tinctoria, Belladonna, Bryonia, Chamomilla, Eupatorium perfoliatum, Ferrum phosphoricum, Gelsemium sempervirens, Pulsatilla, Rhus toxicodendron, Sambucus nigra, Sulphur, Veratrum virede.

Inactive Ingredient

Equal volumes of each ingredient in a Bio-Energetically Enhanced pure water base: 10X, 30X, and LM1 potencies.

Purpose

Uses for fast relief of symptoms:

- fever
- sweats
- chills
- restlessness
- lethargy
- oversensitivity
- muscular soreness
- anxiety

Dosage and Administration

Directions Initially, depress pump until primed. Hold close to mouth and spray one dose directly into mouth. Use 3 times per day. Use additionally as needed.

Adult Dose 3 pump sprays

Children 2-12 years 2 pump sprays

Warnings

If symptoms persist or worsen, or if pregnant or nursing, take only on advice of a healthcare professional. Keep out of reach of children.

Other: Tamper resistant for your protection. Use only if safety seal is intact.

Keep out of reach of children.

Indications and Usage

Uses for fast relief of symptoms: fever, sweats, chills, restlessness, lethargy, nausea, vomiting, irritability, aches, oversensitivity, muscular soreness, and anxiety.

PACKAGE LABEL

King Bio Inc.

3 Westside Dr.

Asheville, NC 28806

Questions? Call 800.543.3245

www.kingbio.com